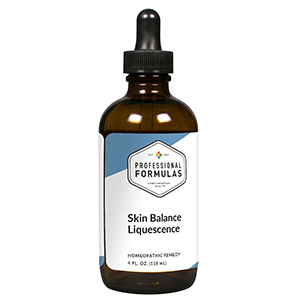 DRUG LABEL: Skin Balance Liquescence
NDC: 63083-3027 | Form: LIQUID
Manufacturer: Professional Complementary Health Formulas
Category: homeopathic | Type: HUMAN OTC DRUG LABEL
Date: 20190815

ACTIVE INGREDIENTS: ANGELICA ARCHANGELICA ROOT 3 [hp_X]/118 mL; BERBERIS VULGARIS ROOT BARK 3 [hp_X]/118 mL; MYRRH 3 [hp_X]/118 mL; GERANIUM MACULATUM ROOT 3 [hp_X]/118 mL; EQUISETUM ARVENSE TOP 3 [hp_X]/118 mL; BERBERIS REPENS ROOT 3 [hp_X]/118 mL; IRIS X GERMANICA ROOT 6 [hp_X]/118 mL; STRYCHNOS NUX-VOMICA SEED 6 [hp_X]/118 mL; THUJA OCCIDENTALIS LEAF 6 [hp_X]/118 mL; HYPERICUM PERFORATUM WHOLE 10 [hp_X]/118 mL; MERCURIUS SOLUBILIS 12 [hp_X]/118 mL; LIQUID PETROLEUM 12 [hp_X]/118 mL; SULFUR 12 [hp_X]/118 mL; GRAPHITE 16 [hp_X]/118 mL
INACTIVE INGREDIENTS: ALCOHOL; WATER

T27

ACTIVE INGREDIENTS

Angelica archangelica 3X
Berberis vulgaris 3X
Myrrha 3X
Geranium maculatum 3X
Equisetum arvense 3X
Mahonia repens 3X
Iris germanica 6X
Nux vomica 6X
Thuja occidentalis 6X
Hypericum perforatum 10X
Mercurius solubilis 12X
Petroleum 12X
Sulphur 12X
Graphites 16X

QUESTIONS

Professional Formulas

PO Box 2034 Lake Oswego, OR 97035

INDICATIONS

For the temporary relief of dry, irritated, red, or itchy skin.*

PURPOSE

*Claims based on traditional homeopathic practice, not accepted medical evidence. Not FDA evaluated.

WARNINGS

Consult a doctor if condition worsens or if symptoms persist. Keep out of the reach of children. In case of overdose, get medical help or contact a poison control center right away. If pregnant or breastfeeding, ask a healthcare professional before use.

Keep out of the reach of children.

PREGNANCY OR BREAST FEEDING

If pregnant or breastfeeding, ask a healthcare professional before use.

DIRECTIONS

Place drops under tongue 30 minutes before/after meals. Adults and children 12 years and over: Take one full dropper up to 2 times per day. Consult a physician for use in children under 12 years of age.

OTHER INFORMATION

Tamper resistant. If seal is broken, do not use. After opening, close container tightly and store at room temperature away from heat.

INACTIVE INGREDIENTS

20% ethanol, purified water.

LABEL

Est 1985

Professional Formulas

Complementary Health

Skin Balance Liquescence

Homeopathic Remedy

4 FL. OZ. (118 mL)